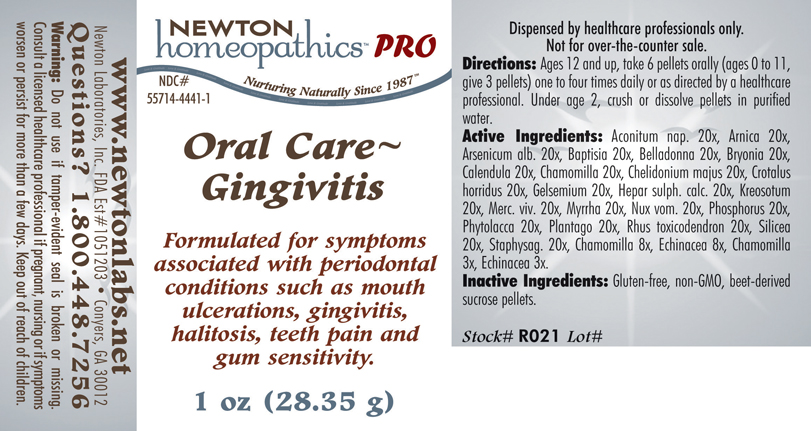 DRUG LABEL: Oral Care - Gingivitis 
NDC: 55714-4441 | Form: PELLET
Manufacturer: Newton Laboratories, Inc.
Category: homeopathic | Type: HUMAN PRESCRIPTION DRUG LABEL
Date: 20110601

ACTIVE INGREDIENTS: Aconitum Napellus 20 [hp_X]/1 g; Arnica Montana 20 [hp_X]/1 g; Arsenic Trioxide 20 [hp_X]/1 g; Baptisia Tinctoria Root 20 [hp_X]/1 g; Atropa Belladonna 20 [hp_X]/1 g; Bryonia Alba Root 20 [hp_X]/1 g; Calendula Officinalis Flowering Top 20 [hp_X]/1 g; Matricaria Recutita 20 [hp_X]/1 g; Chelidonium Majus 20 [hp_X]/1 g; Crotalus Horridus Horridus Venom 20 [hp_X]/1 g; Gelsemium Sempervirens Root 20 [hp_X]/1 g; Calcium Sulfide 20 [hp_X]/1 g; Wood Creosote 20 [hp_X]/1 g; Mercury 20 [hp_X]/1 g; Myrrh 20 [hp_X]/1 g; Strychnos Nux-vomica Seed 20 [hp_X]/1 g; Phosphorus 20 [hp_X]/1 g; Plantago Major 20 [hp_X]/1 g; Toxicodendron Pubescens Leaf 20 [hp_X]/1 g; Silicon Dioxide 20 [hp_X]/1 g; Delphinium Staphisagria Seed 20 [hp_X]/1 g; Echinacea, Unspecified 8 [hp_X]/1 g
INACTIVE INGREDIENTS: Sucrose

Oral Care - Gingivitis

INDICATIONS & USAGE SECTION

Oral Care - Gingivitis Formulated for symptoms associated with periodontal conditions such as mouth ulcerations, gingivitis, halitosis, teeth pain and gum sensitivity.

DOSAGE & ADMINISTRATION SECTION

Directions: Ages 12 and up, take 6 pellets orally (ages 0 to 11, give 3 pellets) one to four times daily or as directed by a healthcare professional. Under age 2, crush or dissolve pellets in purified water.

ACTIVE INGREDIENT SECTION

Aconitum nap. 20x, Arnica 20x, Arsenicum alb. 20x, Baptisia 20x, Belladonna 20x, Bryonia 20x, Calendula 20x, Chamomilla 20x, Chelidonium majus 20x, Crotalus horridus 20x, Gelsemium 20x, Hepar sulph. calc. 20x, Kreosotum 20x, Merc. viv. 20x, Myrrha 20x, Nux vom. 20x, Phosphorus 20x, Phytolacca 20x, Plantago 20x, Rhus toxicodendron 20x, Silicea 20x, Staphysag. 20x, Chamomilla 8x, Echinacea 8x, Chamomilla 3x, Echinacea 3x.

PURPOSE SECTION

Formulated for symptoms associated with periodontal conditions such as mouth ulcerations, gingivitis, halitosis, teeth pain and gum sensitivity.

INACTIVE INGREDIENT SECTION

Inactive Ingredients: Gluten-free, non-GMO, beet-derived sucrose pellets.

QUESTIONS? SECTION

www.newtonlabs.net Newton Laboratories, Inc. FDA Est # 1051203 - Conyers, GA 30012
Questions? 1.800.448.7256

WARNINGS SECTION

Warning: Do not use if tamper - evident seal is broken or missing. Consult a licensed healthcare professional if pregnant, nursing or if symptoms worsen or persist for more than a few days. Keep out of reach of children.

PREGNANCY OR BREAST FEEDING SECTION

Consult a licensed healthcare professional if pregnant, nursing or if symptoms worsen or persist for more than a few days

KEEP OUT OF REACH OF CHILDREN SECTION

Keep out of reach of children